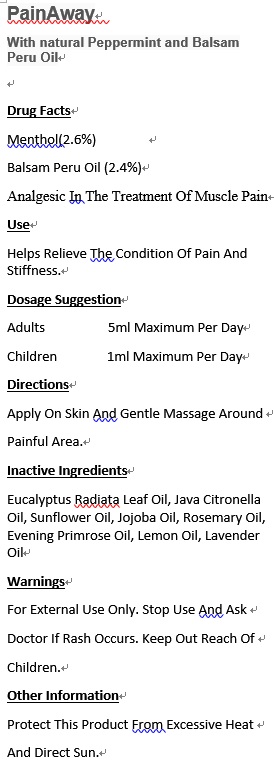 DRUG LABEL: Sleep Disorder Synergy
NDC: 70470-1221 | Form: OIL
Manufacturer: PHYTOPIA CO., LTD.
Category: otc | Type: HUMAN OTC DRUG LABEL
Date: 20180110

ACTIVE INGREDIENTS: BALSAM PERU OIL 1.2 mg/50 mg
INACTIVE INGREDIENTS: EVENING PRIMROSE OIL; JOJOBA OIL; LAVENDER OIL; SWEET MARJORAM OIL; SUNFLOWER OIL; CHAMOMILE FLOWER OIL; GERANIUM OIL, ALGERIAN TYPE

Drug Facts

menthol(2.6%)

Balsam Peru Oil (2.4%)

Analgesic in the treatment of muscle pain

Use

Helps relieve the condition of pain and stiffness.

Dosage Suggestion

Adults 5ml maximum per day

Children 1ml maximum per day

Directions

Apply on skin and gentle massage around painful area.

Inactive Ingredients

EUCALYPTUS RADIATA LEAF OIL, JAVA CITRONELLA OIL, SUNFLOWER OIL, JOJOBA OIL, ROSEMARY OIL, EVENING PRIMROSE OIL, LEMON OIL, LAVENDER OIL

Warnings

For external use only. Stop use and ask doctor if rash occurs. Keep out reach of children.

Other Information

Protect this product from excessive heat

and direct sun.

Warnings

For external use only. Stop use and ask doctor if rash occurs. Keep out reach of children.